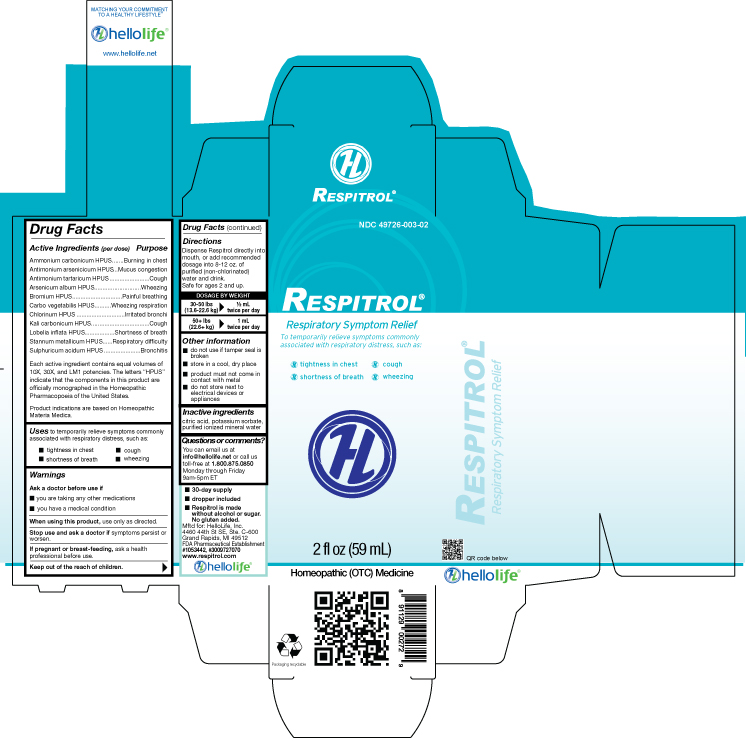 DRUG LABEL: Respitrol
NDC: 49726-003 | Form: LIQUID
Manufacturer: Hello Life, Inc.
Category: homeopathic | Type: HUMAN OTC DRUG LABEL
Date: 20181226

ACTIVE INGREDIENTS: AMMONIUM CARBONATE 10 [hp_X]/59 mL; ANTIMONY ARSENATE 10 [hp_X]/59 mL; ANTIMONY POTASSIUM TARTRATE 10 [hp_X]/59 mL; ARSENIC TRIOXIDE 10 [hp_X]/59 mL; BROMINE 10 [hp_X]/59 mL; ACTIVATED CHARCOAL 10 [hp_X]/59 mL; CHLORINE 10 [hp_X]/59 mL; POTASSIUM CARBONATE 10 [hp_X]/59 mL; LOBELIA INFLATA 10 [hp_X]/59 mL; TIN 10 [hp_X]/59 mL; SULFURIC ACID 10 [hp_X]/59 mL
INACTIVE INGREDIENTS: WATER; POTASSIUM SORBATE; CITRIC ACID MONOHYDRATE

Drug Facts

Active Ingredients (per dose)

Ammonium carbonicum HPUS
Antimonium arsenicicum HPUS
Antimonium tartaricum HPUS
Arsenicum album HPUS
Bromium HPUS
Carbo vegetabilis HPUS
Chlorinum HPUS
Kali carbonicum HPUS
Lobelia inflata HPUS
Stannum metallicum HPUS
Sulphuricum acidum HPUS
Each active ingredient contains equal volumes of 10X, 30X, and LM1 potencies. The letters “HPUS” indicate that the components in this product are officially monographed in the Homeopathic Pharmacopoeia of the United States. Product indications are based on Homeopathic Materia Medica.

Purpose

Ammonium carbonicum HPUS………………….Burning in chest
Antimonium arsenicicum HPUS…………………Mucus congestion
Antimonium tartaricum HPUS……………………Cough
Arsenicum album HPUS………………………….Wheezing
Bromium HPUS……………………………………Asthma
Carbo vegetabilis HPUS……………………….…Wheezing respiration
Chlorinum HPUS…………………………………..Irritated bronchi
Kali carbonicum HPUS……………………………Cough
Lobelia inflata HPUS………………………………Shortness of breath
Stannum metallicum HPUS………………………Respiratory difficulty
Sulphuricum acidum HPUS………………………Bronchitis

Uses

to temporarily relieve minor symptoms commonly associated with asthma, such as:

- tightness in chest
- cough
- shortness of breath
- wheezing

Warnings

Ask a doctor before use if

- you are taking other medications
- you have a medical condition

When using this product, use only as directed.

Stop use and ask a doctor if symptoms persist or worsen.

PREGNANCY OR BREAST FEEDING

If pregnant or breast-feeding, ask a health professional before use.

Keep out of the reach of children.

Directions

Dispense Respitrol directly into mouth, or add recommended dosage into 8-12 oz. of purified (non-chlorinated) water and drink. Safe for ages 2 and up.

DOSAGE BY WEIGHT
30-50 lbs 1/2 mL
(13.6-22.6 kg) twice per day
50+ lbs 1 mL
(22.6+ kg) twice per day

Other information

- do not use if tamper seal is broken
- store in a cool, dry place
- product must not come in contact with metal
- do not store next to electrical devices or appliances

Inactive ingredients

citric acid, potassium sorbate, purified ionized mineral water

Questions or comments?

You can email us at info@hellolife.net or call us toll-free at 1.800.875.0850 Monday through Friday 9am-5pm ET

DESCRIPTION

- 30-day supply
- dropper included
- Respitrol is made without alcohol or sugar. No gluten added.

Mftd for: HelloLife, LLC
4460 44th St SE, Ste. C-600
Grand Rapids, MI 49512
FDA Pharmaceutical Establishment
#1053442 #3009727070
www.respitrol.com

Principal Display Panel

NDC 49726-003-02

RespitrolTM

Asthma Symptom Relief

To temporarily relieve minor symptoms commonly associated with asthma, such as:

- tightness in chest
- cough
- shortness of breath
- wheezing

2 fl oz (59 mL)
Homeopathic (OTC) Medicine